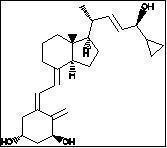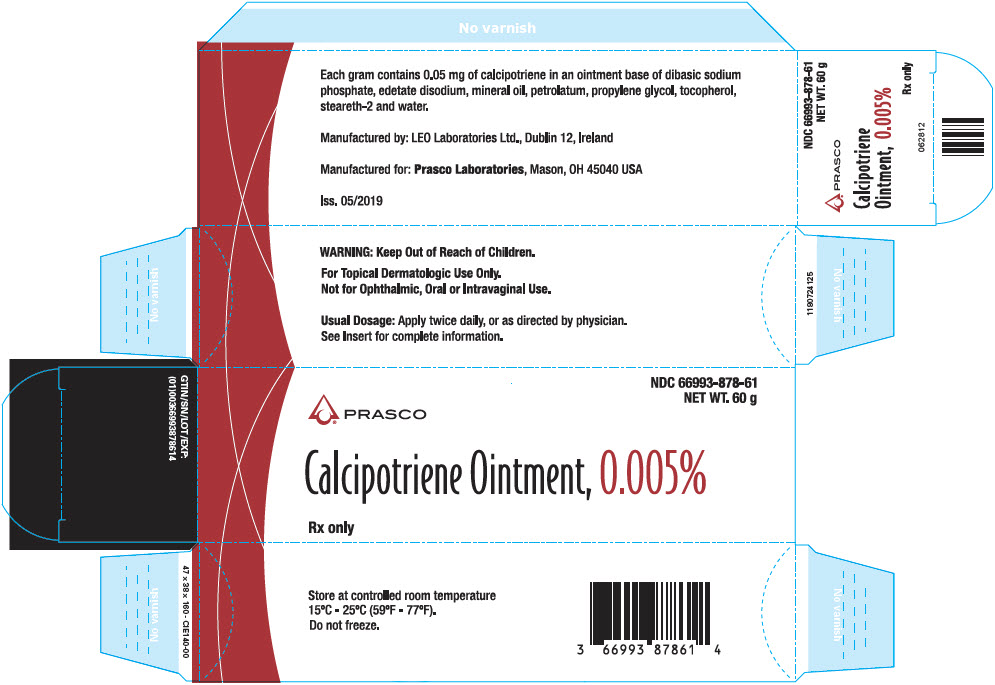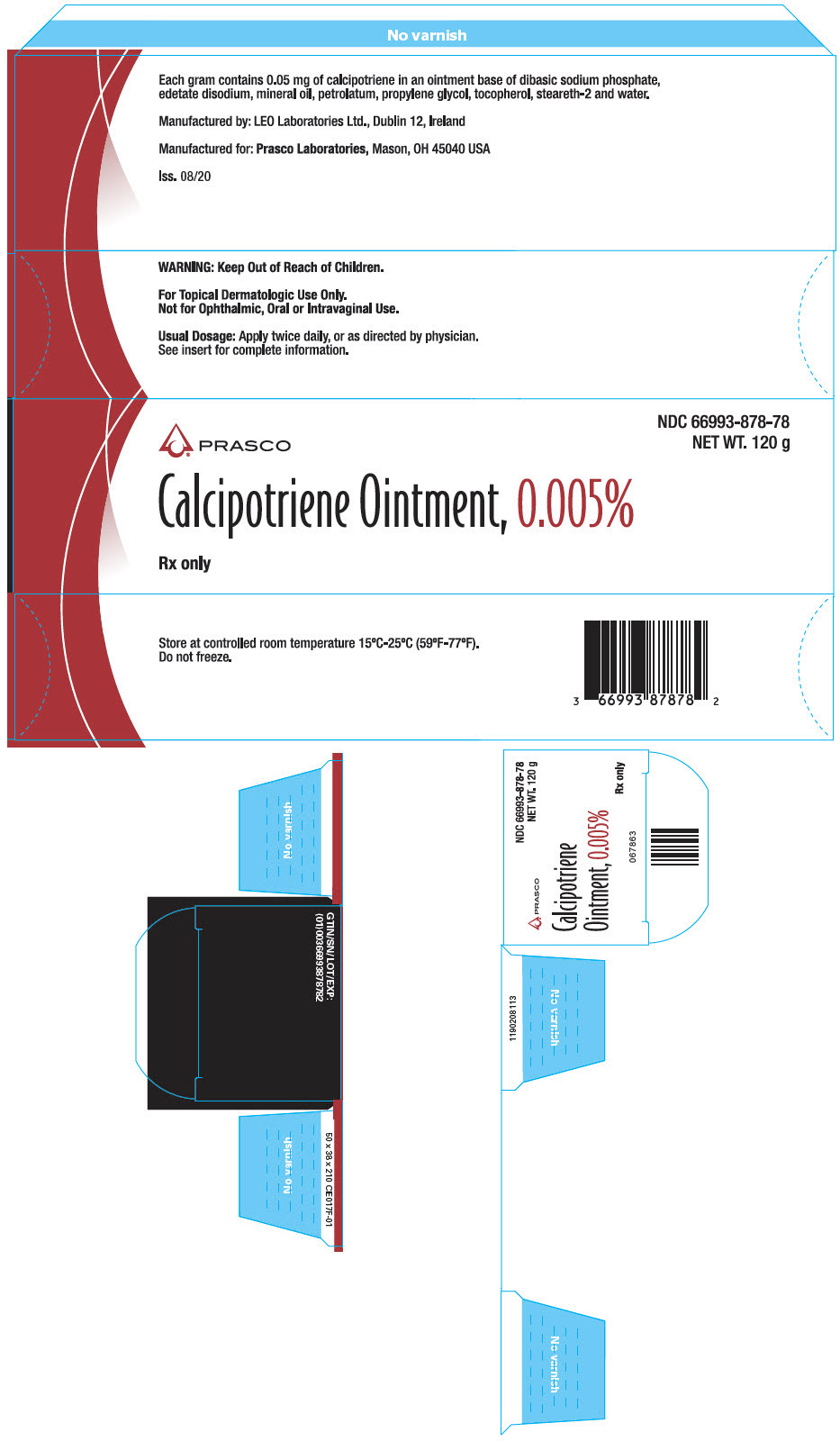 DRUG LABEL: calcipotriene
NDC: 66993-878 | Form: OINTMENT
Manufacturer: Prasco Laboratories
Category: prescription | Type: HUMAN PRESCRIPTION DRUG LABEL
Date: 20200807

ACTIVE INGREDIENTS: CALCIPOTRIENE 50 ug/1 g
INACTIVE INGREDIENTS: SODIUM PHOSPHATE, DIBASIC, UNSPECIFIED FORM; EDETATE DISODIUM; MINERAL OIL; PETROLATUM; PROPYLENE GLYCOL; .ALPHA.-TOCOPHEROL; STEARETH-2; WATER

Calcipotriene Ointment, 0.005%
FOR TOPICAL DERMATOLOGIC USE ONLY.
Not for Ophthalmic, Oral or Intravaginal Use.
Rx only

DESCRIPTION

Calcipotriene Ointment, 0.005% contains the compound calcipotriene, a synthetic vitamin D3 derivative, for topical dermatological use.

Chemically, calcipotriene is (5Z,7E,22E,24S)-24-cyclopropyl-9,10-secochola-5,7,10(19),22-tetraene-1α,3β,24-triol-, with the empirical formula C27H40O3, a molecular weight of 412.6, and the following structural formula:

Calcipotriene is a white or off-white crystalline substance. Calcipotriene Ointment contains calcipotriene 50 μg/g in an ointment base of dibasic sodium phosphate, edetate disodium, mineral oil, petrolatum, propylene glycol, tocopherol, steareth-2 and water.

CLINICAL PHARMACOLOGY

In humans, the natural supply of vitamin D depends mainly on exposure to the ultraviolet rays of the sun for conversion of 7-dehydrocholesterol to vitamin D3 (cholecalciferol) in the skin. Calcipotriene is a synthetic analog of vitamin D3.

Clinical studies with radiolabelled Calcipotriene Ointment indicate that approximately 6% (± 3%, SD) of the applied dose of calcipotriene is absorbed systemically when the ointment is applied topically to psoriasis plaques, or 5% (± 2.6%, SD) when applied to normal skin, and much of the absorbed active is converted to inactive metabolites within 24 hours of application.

Vitamin D and its metabolites are transported in the blood, bound to specific plasma proteins. The active form of the vitamin, 1,25-dihydroxy vitamin D3 (calcitriol), is known to be recycled via the liver and excreted in the bile. Calcipotriene metabolism following systemic uptake is rapid, and occurs via a similar pathway to the natural hormone. The primary metabolites are much less potent than the parent compound.

There is evidence that maternal 1,25-dihydroxy vitamin D3 (calcitriol) may enter the fetal circulation, but it is not known whether it is excreted in human milk. The systemic disposition of calcipotriene is expected to be similar to that of the naturally occurring vitamin.

CLINICAL STUDIES

Adequate and well-controlled trials of patients treated with Calcipotriene Ointment have demonstrated improvement usually beginning after 2 weeks of therapy. This improvement continued in patients using Calcipotriene Ointment once daily and twice daily. After 8 weeks of once daily Calcipotriene Ointment, 56.7% of patients showed at least marked improvements (6.4% showed complete clearing). After 8 weeks of twice daily Calcipotriene Ointment, 70.0% of patients showed at least marked improvement (11.3% showed complete clearing).

Subtracting percentages of patients using placebo (vehicle only) from percentages of patients using Calcipotriene Ointment who had at least marked improvements after 8 weeks yields 39.9% for once daily and 49.6% for twice daily. This adjustment for placebo effect indicates that what might appear to be differences between once and twice daily use may reflect differences in the studies independent from the frequency of dosing. Although there was a numerical difference in comparison across studies, twice daily dosing has not been shown to be superior in efficacy to once daily dosing.

Over 400 patients have been treated in open label clinical studies of Calcipotriene Ointment for periods of up to one year. In half of these studies, patients who previously had not responded well to Calcipotriene Ointment were excluded. The adverse events in these extended studies included skin irritation in approximately 25% of patients and worsening of psoriasis in approximately 10% of patients. In one of these open label studies, half of the patients no longer required Calcipotriene Ointment by 16 weeks of treatment, because of satisfactory therapeutic results.

INDICATIONS AND USAGE

Calcipotriene Ointment, 0.005%, is indicated for the treatment of plaque psoriasis in adults. The safety and effectiveness of topical calcipotriene in dermatoses other than psoriasis have not been established.

CONTRAINDICATIONS

Calcipotriene Ointment is contraindicated in those patients with a history of hypersensitivity to any of the components of the preparation. It should not be used by patients with demonstrated hypercalcemia or evidence of vitamin D toxicity. Calcipotriene Ointment should not be used on the face.

WARNINGS

Contact dermatitis, including allergic contact dermatitis, has been observed with the use of Calcipotriene Ointment.

PRECAUTIONS

General

Use of Calcipotriene Ointment may cause irritation of lesions and surrounding uninvolved skin. If irritation develops, Calcipotriene Ointment should be discontinued.

For external use only. Keep out of the reach of children. Always wash hands thoroughly after use.

Transient, rapidly reversible elevation of serum calcium has occurred with use of Calcipotriene Ointment. If elevation in serum calcium outside the normal range should occur, discontinue treatment until normal calcium levels are restored.

Information for Patients

Patients using Calcipotriene Ointment should receive the following information and instructions:

1. This medication is to be used as directed by the physician. It is for external use only. Avoid contact with the face or eyes. As with any topical medication, patients should wash hands after application.
2. This medication should not be used for any disorder other than that for which it was prescribed.
3. Patients should report to their physician any signs of local adverse reactions.
4. Patients that apply Calcipotriene Ointment to exposed portions of the body should avoid excessive exposure to either natural or artificial sunlight (including tanning booths, sun lamps, etc.).

Carcinogenesis, Mutagenesis, Impairment of Fertility

When calcipotriene was applied topically to mice for up to 24 months at dosages of 3, 10 and 30 μg/kg/day (corresponding to 9, 30 and 90 μg/m^2/day), no significant changes in tumor incidence were observed when compared to control. In a study in which albino hairless mice were exposed to both UVR and topically applied calcipotriene, a reduction in the time required for UVR to induce the formation of skin tumors was observed (statistically significant in males only), suggesting that calcipotriene may enhance the effect of UVR to induce skin tumors. Patients that apply Calcipotriene Ointment to exposed portions of the body should avoid excessive exposure to either natural or artificial sunlight (including tanning booths, sun lamps, etc.). Physicians may wish to avoid use of phototherapy in patients that use Calcipotriene Ointment.

Calcipotriene did not elicit any mutagenic effects in an Ames mutagenicity assay, a mouse lymphoma TK locus assay, a human lymphocyte chromosome aberration assay, or in a micronucleus assay conducted in mice.

Studies in rats at doses up to 54 μg/kg/day (324 μg/m^2/day) of calcipotriene indicated no impairment of fertility or general reproductive performance.

Pregnancy

Teratogenic Effects

Studies of teratogenicity were done by the oral route where bioavailability is expected to be approximately 40-60% of the administered dose. In rabbits, increased maternal and fetal toxicity were noted at a dosage of 12 μg/kg/day (132 μg/m^2/day); a dosage of 36 μg/kg/day (396 μg/m^2/day) resulted in a significant increase in the incidence of incomplete ossification of the pubic bones and forelimb phalanges of fetuses. In a rat study, a dosage of 54 μg/kg/day (318 μg/m^2/day) resulted in a significantly increased incidence of skeletal abnormalities (enlarged fontanelles and extra ribs). The enlarged fontanelles are most likely due to calcipotriene's effect upon calcium metabolism. The estimated maternal and fetal no-effect exposure levels in the rat (43.2 μg/m2/day) and rabbit (17.6 μg/m^2/day) studies are approximately equal to the expected human systemic exposure level (18.5 μg/m^2/day) from dermal application. There are no adequate and well-controlled studies in pregnant women. Therefore, Calcipotriene Ointment should be used during pregnancy only if the potential benefit justifies the potential risk to the fetus.

Nursing Mothers

It is not known whether calcipotriene is excreted in human milk. Because many drugs are excreted in human milk, caution should be exercised when Calcipotriene Ointment, 0.005% is administered to a nursing woman.

Pediatric Use

Safety and effectiveness of Calcipotriene Ointment in pediatric patients have not been established. Because of a higher ratio of skin surface area to body mass, pediatric patients are at greater risk than adults of systemic adverse effects when they are treated with topical medication.

Geriatric Use

Of the total number of patients in clinical studies of calcipotriene ointment, approximately 12% were 65 or older, while approximately 4% were 75 and over. The results of an analysis of severity of skin-related adverse events showed a statistically significant difference for subjects over 65 years (more severe) compared to those under 65 years (less severe).

ADVERSE REACTIONS

Clinical Trials Experience

In controlled clinical trials, the most frequent adverse reactions reported for Calcipotriene Ointment were burning, itching and skin irritation, which occurred in approximately 10-15% of patients.

Erythema, dry skin, peeling, rash, dermatitis, worsening of psoriasis including development of facial/scalp psoriasis were reported in 1 to 10% of patients. Other experiences reported in less than 1% of patients included skin atrophy, hyperpigmentation, hypercalcemia, and folliculitis. Once daily dosing has not been shown to be superior in safety to twice daily dosing.

Postmarketing Experience

Because these reactions are reported voluntarily from a population of uncertain size, it is not always possible to reliably estimate their frequency or establish a causal relationship to drug exposure.

The following adverse reactions associated with the use of Calcipotriene Ointment have been identified post-approval: contact dermatitis, including allergic contact dermatitis.

OVERDOSAGE

Topically applied Calcipotriene Ointment can be absorbed in sufficient amounts to produce systemic effects. Elevated serum calcium has been observed with excessive use of Calcipotriene Ointment.

DOSAGE AND ADMINISTRATION

Apply a thin layer of Calcipotriene Ointment once or twice daily and rub in gently and completely.

HOW SUPPLIED

Calcipotriene Ointment, 0.005% is available in:

60 gram aluminum tubes NDC 66993-878-61

120 gram aluminum tubes NDC 66993-878-78

STORAGE

Store at controlled room temperature 15°C-25°C (59°F-77°F). Do not freeze.

Manufactured for:

Prasco Laboratories

Mason, OH 45040 USA

Manufactured by:

LEO Laboratories Ltd., Dublin 12,

Ireland

To report SUSPECTED ADVERSE REACTIONS, contact LEO Pharma Inc. at 1-877-494-4536 or FDA at 1-800-FDA-1088 or www.fda.gov/medwatch.

Revised 06/2019

PRINCIPAL DISPLAY PANEL - 60 g Tube Carton

NDC 66993-878-61
NET WT. 60 g

PRASCO

Calcipotriene Ointment, 0.005%

Rx only

PRINCIPAL DISPLAY PANEL - 120 g Tube Carton

PRASCO

NDC 66993-878-78
NET WT. 120 g

Calcipotriene Ointment, 0.005%

Rx only